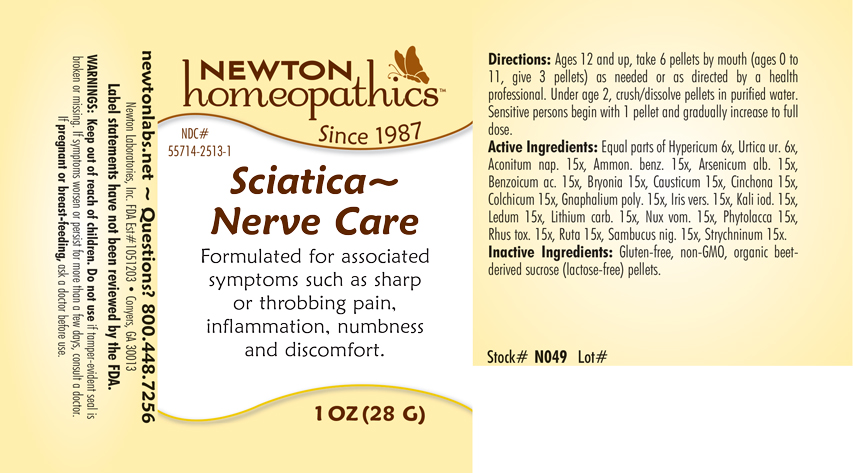 DRUG LABEL: Sciatica-Nerve Care
NDC: 55714-2513 | Form: PELLET
Manufacturer: Newton Laboratories, Inc.
Category: homeopathic | Type: HUMAN OTC DRUG LABEL
Date: 20250210

ACTIVE INGREDIENTS: ACONITUM NAPELLUS 15 [hp_X]/1 g; AMMONIUM BENZOATE 15 [hp_X]/1 g; ARSENIC TRIOXIDE 15 [hp_X]/1 g; BENZOIC ACID 15 [hp_X]/1 g; BRYONIA ALBA ROOT 15 [hp_X]/1 g; CAUSTICUM 15 [hp_X]/1 g; CINCHONA OFFICINALIS BARK 15 [hp_X]/1 g; COLCHICUM AUTUMNALE BULB 15 [hp_X]/1 g; PSEUDOGNAPHALIUM OBTUSIFOLIUM 15 [hp_X]/1 g; IRIS VERSICOLOR ROOT 15 [hp_X]/1 g; POTASSIUM IODIDE 15 [hp_X]/1 g; RHODODENDRON TOMENTOSUM LEAFY TWIG 15 [hp_X]/1 g; LITHIUM CARBONATE 15 [hp_X]/1 g; STRYCHNOS NUX-VOMICA SEED 15 [hp_X]/1 g; PHYTOLACCA AMERICANA ROOT 15 [hp_X]/1 g; TOXICODENDRON PUBESCENS LEAF 15 [hp_X]/1 g; RUTA GRAVEOLENS FLOWERING TOP 15 [hp_X]/1 g; SAMBUCUS NIGRA FLOWERING TOP 15 [hp_X]/1 g; STRYCHNINE 15 [hp_X]/1 g; HYPERICUM PERFORATUM 6 [hp_X]/1 g; URTICA URENS 6 [hp_X]/1 g
INACTIVE INGREDIENTS: SUCROSE

Sciatica 2513P

INDICATIONS & USAGE SECTION

Formulated for associated symptoms such as sharp or throbbing pain, Inflammation, numbness and discomfort.

DOSAGE & ADMINISTRATION SECTION

Directions: Ages 12 and up, take 6 pellets by mouth (ages 0 to 11, give 3 pellets) as needed or as directed by a health professional. Under age 2, crush/dissolve pellets in purified water. Sensitive persons begin with 1 pellet and gradually increase to full dose.

OTC - ACTIVE INGREDIENT SECTION

Equal parts of Hypericum perforatum 6x, Urtica urens 6x, Aconitum napellus 15x, Ammonium benzoicum 15x, Arsenicum album 15x, Benzoicum acidum 15x, Bryonia 15x, Causticum 15x, Cinchona officinalis 15x, Colchicum autumnale 15x, Gnaphalium polycephalum 15x, Iris versicolor 15x, Kali iodatum 15x, Ledum palustre 15x, Lithium carbonicum 15x, Nux vomica 15x, Phytolacca decandra 15x, Rhus toxicodendron 15x, Ruta graveolens 15x, Sambucus nigra 15x, Strychninum 15x.

OTC - PURPOSE SECTION

Formulated for associated symptoms such as sharp or throbbing pain, Inflammation, numbness and discomfort.

INACTIVE INGREDIENT SECTION

Inactive Ingredients: Gluten-free, non-GMO, organic beet-derived sucrose (lactose-free) pellets.

QUESTIONS SECTION

newtonlabs.net – Questions? 800.448.7256

Newton Laboratories, Inc. FDA Est # 1051203 - Conyers, GA 30013

WARNINGS SECTION

WARNINGS: Keep out of reach of children. Do not use if tamper-evident seal is broken or missing. If symptoms worsen or persist for more than a few days, consult a doctor. If pregnant or breast-feeding, ask a doctor before use.

OTC - PREGNANCY OR BREAST FEEDING SECTION

If pregnant or breast-feeding, ask a doctor before use.

OTC - KEEP OUT OF REACH OF CHILDREN SECTION

Keep out of reach of children.